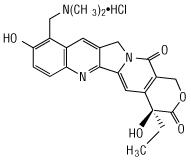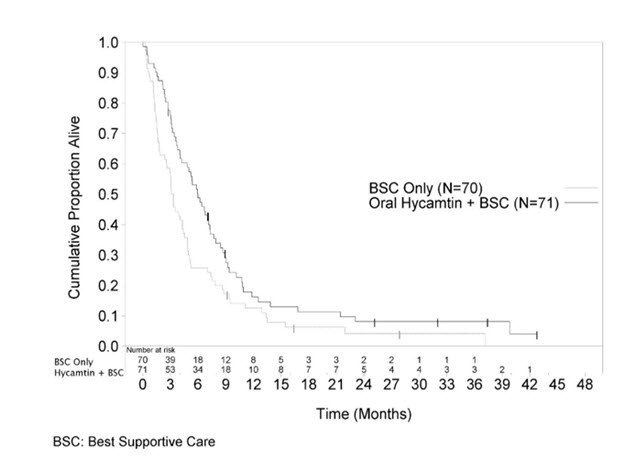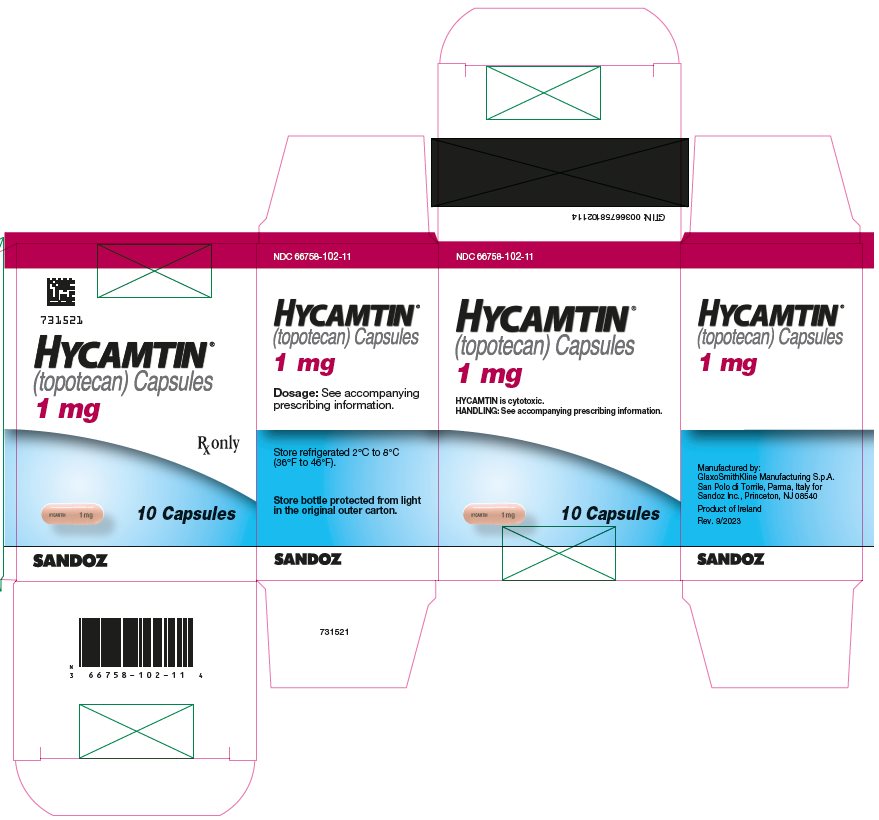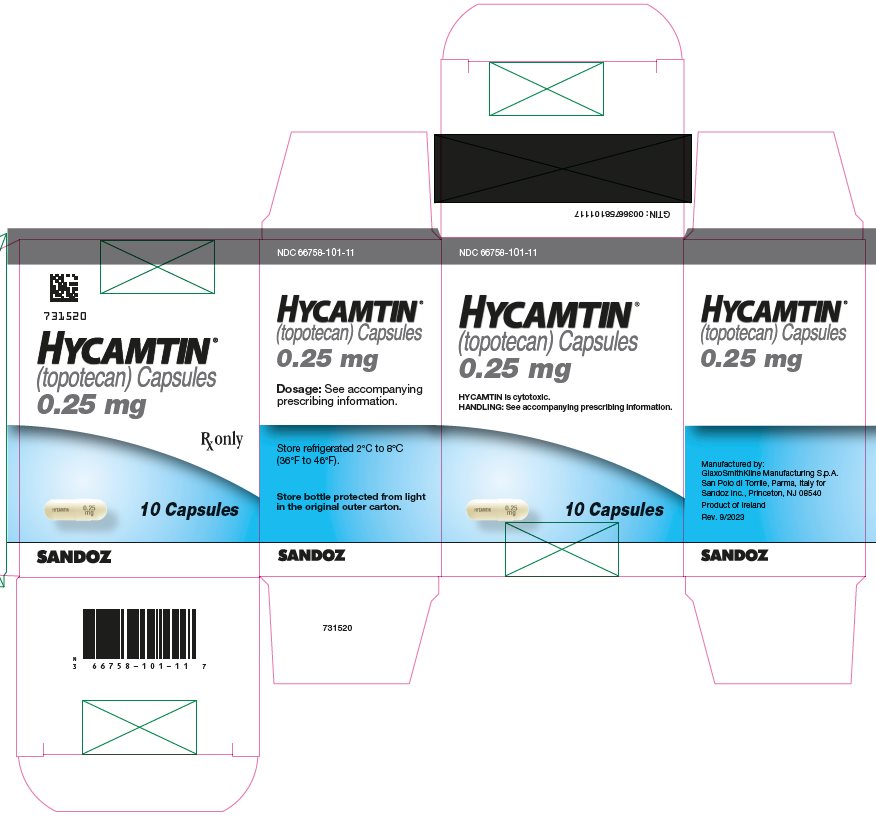 DRUG LABEL: HYCAMTIN
NDC: 66758-101 | Form: CAPSULE
Manufacturer: Sandoz Inc
Category: prescription | Type: HUMAN PRESCRIPTION DRUG LABEL
Date: 20230918

ACTIVE INGREDIENTS: TOPOTECAN HYDROCHLORIDE .25 mg/1 1
INACTIVE INGREDIENTS: GLYCERYL MONOSTEARATE; GELATIN, UNSPECIFIED; TITANIUM DIOXIDE; FERRIC OXIDE RED; HYDROGENATED PALM OIL

HIGHLIGHTS OF PRESCRIBING INFORMATION

These highlights do not include all the information needed to use HYCAMTIN CAPSULES safely and effectively. See full prescribing information for HYCAMTIN CAPSULES.
HYCAMTIN® (topotecan) capsules, for oral use
Initial U.S. Approval: 1996

WARNING: MYELOSUPPRESSION

See full prescribing information for complete boxed warning.

HYCAMTIN can cause severe myelosuppression. Administer first cycle only to patients with baseline neutrophil counts of greater than or equal to 1,500/mm^3 and platelet counts of greater than or equal to 100,000/mm^3. Monitor blood cell counts (2.2, 5.1).

1 INDICATIONS AND USAGE

HYCAMTIN capsules is a topoisomerase inhibitor indicated for treatment of patients with relapsed small cell lung cancer (SCLC). (1)

2 DOSAGE AND ADMINISTRATION

- The recommended dosage is 2.3 mg/m^2/day orally once daily for 5 consecutive days starting on Day 1 of a 21-day cycle. (2.1)
- Renal Impairment: Reduce dose if creatinine clearance (CLcr) less than 50 mL/min. (2.3)

3 DOSAGE FORMS AND STRENGTHS

Capsules: 0.25 mg or 1 mg (3)

4 CONTRAINDICATIONS

- History of severe hypersensitivity reactions to topotecan (4)

5 WARNINGS AND PRECAUTIONS

- Diarrhea: Severe diarrhea can occur. Withhold and reduce dose as recommended. (2.2, 5.2)
- Interstitial Lung Disease (ILD): Fatal cases have occurred. Permanently discontinue if confirmed ILD. (5.3)
- Embryo-Fetal Toxicity: Can cause fetal harm. Advise patients of potential risk to the fetus and to use effective contraception. (5.4, 8.1, 8.3)

6 ADVERSE REACTIONS

- The most common Grade 3 or 4 hematologic adverse reactions (incidence > 20%) were neutropenia, anemia, and thrombocytopenia.
- The most common (incidence > 10%) non-hematologic adverse reactions (all Grades) were nausea, diarrhea, vomiting, alopecia, fatigue, and anorexia. (6.1)

To report SUSPECTED ADVERSE REACTIONS, contact Sandoz Inc. at 1-800-525-8747 or FDA at 1-800-FDA-1088 or www.fda.gov/medwatch.

7 DRUG INTERACTIONS

- Avoid concomitant use of P-glycoprotein (P-gp) or breast cancer resistance protein (BCRP) inhibitors with HYCAMTIN capsules. (7.1, 12.3)

8 USE IN SPECIFIC POPULATIONS

- Lactation: Advise not to breastfeed. (8.2)

FULL PRESCRIBING INFORMATION

WARNING: MYELOSUPPRESSION

HYCAMTIN can cause severe myelosuppression. Administer first cycle only to patients with baseline neutrophil counts of greater than or equal to 1,500/mm^3 and platelet counts greater than or equal to 100,000/mm^3. Monitor blood cell counts [see Warnings and Precautions (5.1)].

1 INDICATIONS AND USAGE

HYCAMTIN® capsules are indicated for the treatment of relapsed small cell lung cancer (SCLC) in patients with a prior complete or partial response and who are at least 45 days from the end of first-line chemotherapy.

2 DOSAGE AND ADMINISTRATION

2.1 Recommended Dosage

The recommended dosage of HYCAMTIN capsules is 2.3 mg/m^2/day orally once daily, with or without food, for 5 consecutive days, starting on Day 1 of a 21-day cycle. Round the dose to the nearest 0.25 mg and prescribe the minimum number of 1 mg and 0.25 mg capsules. Prescribe the same number of capsules for each of the 5 dosing days.

Swallow capsules whole. Do not chew, crush, or divide the capsules.

If a dose of HYCAMTIN capsules is missed or vomiting occurs after taking a dose, do not administer an additional dose and take the next dose at the scheduled time.

2.2 Dosage Modifications for Adverse Reactions

Diarrhea

Do not administer HYCAMTIN capsules to patients with Grade 3 or 4 diarrhea. After recovery to Grade 1 or less, reduce the dose by 0.4 mg/m^2/day for subsequent courses [see Warnings and Precautions (5.2)].

Hematologic

Do not administer subsequent cycles of HYCAMTIN capsules until neutrophils recover to greater than 1,000/mm^3, platelets recover to greater than 100,000/mm^3, and hemoglobin levels recover to greater than or equal to 9 g/dL (with transfusion if necessary) [see Warnings and Precautions (5.1)].

Reduce dose by 0.4 mg/m^2/day for:

- neutrophil counts of less than 500/mm^3 associated with fever or infection or lasting for 7 days or more;
- neutrophil counts of 500 to 1,000/mm^3 lasting beyond day 21 of the treatment course; or
- platelet counts less than 25,000/mm^3.

2.3 Dosage Modifications for Renal Impairment

Reduce the dose of HYCAMTIN capsules in patients with the following creatinine clearance (CLcr), calculated with the Cockcroft-Gault method using ideal body weight.
2. CLcr 30 to 49 mL/min: Administer 1.5 mg/m^2/day.
3. CLcr less than 30 mL/min: Administer 0.6 mg/m^2/day.

3 DOSAGE FORMS AND STRENGTHS

Capsules

- 0.25 mg: opaque white to yellowish-white and imprinted with HYCAMTIN and 0.25 mg.
- 1 mg: opaque pink and imprinted with HYCAMTIN and 1 mg.

4 CONTRAINDICATIONS

HYCAMTIN is contraindicated in patients who have a history of severe hypersensitivity reactions to topotecan. Reactions have included anaphylactoid reactions [see Adverse Reactions (6.2)].

5 WARNINGS AND PRECAUTIONS

5.1 Myelosuppression

HYCAMTIN can cause severe myelosuppression. The following safety data are based on an integrated safety database from four trials in patients with lung cancer (N = 682) who received HYCAMTIN capsules at a dose of 2.3 mg/m^2 orally once daily for 5 consecutive days, starting on Day 1 of a 21-day cycle.

The median day for neutrophil and platelet nadirs occurred on Day 15. Grade 4 neutropenia occurred in 32% of the 682 patients, with a median duration of 7 days. Grade 4 neutropenia most commonly occurred during cycle 1 (20% of patients). Clinical sequelae of neutropenia included infection (17%), febrile neutropenia (4%), sepsis (2%), and septic death (1%). Grade 4 thrombocytopenia occurred in 6%, with a median duration of 3 days. Grade 3 or 4 anemia occurred in 25%.

HYCAMTIN can cause fatal typhlitis (neutropenic enterocolitis). Consider the possibility of typhlitis in patients presenting with fever, neutropenia, and abdominal pain.

Administer the first cycle of HYCAMTIN capsules only to patients with a baseline neutrophil count greater than or equal to 1,500/mm^3 and a platelet count greater than or equal to 100,000/mm^3. Monitor blood cell counts frequently during treatment. Withhold and reduce dose of HYCAMTIN capsules based on neutrophil counts, platelet counts and hemoglobin levels [see Dosage and Administration (2.2)].

5.2 Diarrhea

Diarrhea, including severe and life-threatening diarrhea requiring hospitalization, can occur with HYCAMTIN capsules. Diarrhea can occur at the same time as drug-induced neutropenia and its sequelae. In the 682 patients who received HYCAMTIN capsules in the four lung cancer trials, the incidence of diarrhea caused by HYCAMTIN capsules was 22%, including Grade 3 (4%) and Grade 4 (0.4%). The incidence of Grade 3 or 4 diarrhea proximate (within 5 days) to Grade 3 or 4 neutropenia was 5%. The median time to onset of Grade 2 to 4 diarrhea was 9 days in the group receiving HYCAMTIN capsules.

Monitor patients for diarrhea and treat with antidiarrheals at the first sign of diarrhea. Withhold and dose reduce as recommended based on severity [see Dosage and Administration (2.2)].

5.3 Interstitial Lung Disease

Interstitial lung disease (ILD), including fatalities, can occur with HYCAMTIN. Underlying risk factors include history of ILD, pulmonary fibrosis, lung cancer, thoracic radiation, and use of pneumotoxic drugs or colony stimulating factors.

Monitor for pulmonary symptoms indicative of ILD. Permanently discontinue HYCAMTIN capsules if ILD is confirmed.

5.4 Embryo-Fetal Toxicity

Based on animal data, HYCAMTIN can cause fetal harm when administered to a pregnant woman. Topotecan caused embryolethality, fetotoxicity, and teratogenicity in rats and rabbits when administered during organogenesis. Advise women of the potential risk to fetus. Advise females of reproductive potential to use effective contraception during treatment and for at least 6 months after the last dose of HYCAMTIN capsules. Advise males with a female partner of reproductive potential to use effective contraception during treatment with HYCAMTIN capsules and for 3 months after the last dose [see Use in Specific Populations (8.1, 8.3), Nonclincial Toxicology (13.1)].

6 ADVERSE REACTIONS

The following serious adverse reactions are described elsewhere in the labeling:

- Myelosuppression [see Warnings and Precautions (5.1)]
- Diarrhea [see Warnings and Precautions (5.2)]
- Interstitial Lung Disease (ILD) [see Warnings and Precautions (5.3)]

6.1 Clinical Trials Experience

Because clinical trials are conducted under widely varying conditions, adverse reaction rates observed in the clinical trials of a drug cannot be directly compared with rates in the clinical trials of another drug and may not reflect the rates observed in practice.

The data in the Warnings and Precautions and below reflects exposure to HYCAMTIN capsules in 682 patients with recurrent lung cancer enrolled in four randomized, open label trials, including 275 patients with small lung cell lung cancer (SCLC) (Studies 478, 065 and 396), and 407 patients with non-small cell lung cancer (NSCLC) (Study 387), who received at least one dose of HYCAMTIN capsules. Patients in these trials had advanced lung cancer and received prior chemotherapy in the first-line setting. Patients received HYCAMTIN capsules 2.3 mg/m^2 orally once daily for 5 consecutive days, starting on Day 1 of a 21-day cycle. The median number of cycles was 3 (range: 1 to 20).

The safety of HYCAMTIN capsules was evaluated in a randomized trial (Study 478) conducted in 70 patients with recurrent SCLC [see Clinical Studies (14)].

In the 682 patients who received HYCAMTIN capsules in the four lung cancer trials, 39 deaths (6%) occurred within 30 days after the last dose for a reason other than progressive disease: 13 due to hematologic toxicity, 5 due to non-hematologic toxicity (2 from diarrhea), and 21 due to other causes.

Table 1 describes the hematologic and non-hematologic adverse reactions that occurred in greater than 5% of patients treated with HYCAMTIN capsules in these trials.

Table 1. Adverse Reactions Occurring in Greater than or Equal to 5% of Patients With Lung Cancer
Adverse Reactions [Adverse reactions were graded using National Cancer Institute (NCI) Common Toxicity Criteria (CTC) Version 2.0.] | HYCAMTIN Capsules With Best Supportive Care (Study 478) |  |  | HYCAMTIN Capsules Lung Cancer Population (Studies 478, 065, 396 and 387)
Adverse Reactions [Adverse reactions were graded using National Cancer Institute (NCI) Common Toxicity Criteria (CTC) Version 2.0.] | N = 70 |  |  | N = 682
Adverse Reactions [Adverse reactions were graded using National Cancer Institute (NCI) Common Toxicity Criteria (CTC) Version 2.0.] | All Grades; (%) | Grade 3; (%) | Grade 4; (%) | All Grades; (%) | Grade 3; (%) | Grade 4; (%)
Hematologic
Anemia | 94 | 15 | 10 | 98 | 18 | 7
Neutropenia | 91 | 28 | 33 | 83 | 24 | 32
Thrombocytopenia | 81 | 30 | 7 | 81 | 29 | 6
Non-hematologic
Nausea | 27 | 1 | 0 | 33 | 3 | 0
Vomiting | 19 | 1 | 0 | 21 | 3 | 0.4
Diarrhea | 14 | 4 | 1 | 22 | 4 | 0.4
Fatigue | 11 | 0 | 0 | 19 | 4 | 0.1
Alopecia | 10 | 0 | 0 | 20 | 0.1 | 0
Pyrexia | 7 | 1 | 0 | 5 | 1 | 1
Anorexia | 7 | 0 | 0 | 14 | 2 | 0
Asthenia | 3 | 0 | 0 | 7 | 2 | 0

6.2 Postmarketing Experience

The following reactions have been identified during post approval use of HYCAMTIN. Because these reactions are reported voluntarily from a population of unknown size, it is not always possible to reliably estimate their frequency or establish a causal relationship to drug exposure.

Gastrointestinal: Gastrointestinal perforation
General and Administration Site Conditions: Mucosal inflammation Hypersensitivity: Allergic manifestations, anaphylactoid reactions, angioedema

7 DRUG INTERACTIONS

7.1 Effect of Other Drugs on HYCAMTIN

P-glycoprotein or Breast Cancer Resistance Protein Inhibitor

Concomitant use of a P-glycoprotein (P-gp) or breast cancer resistance protein (BCRP) inhibitor increases topotecan AUC [see Clinical Pharmacology (12.3)], which may increase the risk of adverse reactions. Avoid concomitant use HYCAMTIN capsules with P-gp inhibitors or BCRP inhibitors.

8 USE IN SPECIFIC POPULATIONS

8.1 Pregnancy

Risk Summary

Based on animal data and its mechanism of action, HYCAMTIN can cause fetal harm when administered to a pregnant woman. There are no available clinical data on the use of HYCAMTIN in pregnancy. Topotecan caused embryolethality, fetotoxicity, and teratogenicity in rats and rabbits when administered during organogenesis at doses similar to the clinical dose (see Data). Advise pregnant women of the potential risk to a fetus.

In the U.S. general population, the background risk of major birth defects is 2% to 4% and of miscarriage is 15% to 20% of clinically recognized pregnancies.

Data

Animal Data

In rabbits, an intravenous dose of 0.10 mg/kg/day [about equal to the 1.5 mg/m^2 clinical intravenous dose based on body surface area (BSA)] given on days 6 through 20 of gestation caused maternal toxicity, embryolethality, and reduced fetal body weight. In the rat, an intravenous dose of 0.23 mg/kg/day (about equal to the 1.5 mg/m^2 clinical intravenous dose based on BSA) given for 14 days before mating through gestation day 6 caused fetal resorption, microphthalmia, pre-implant loss, and mild maternal toxicity. Administration of an intravenous dose of 0.10 mg/kg/day (about half the 1.5 mg/m^2 clinical intravenous dose based on BSA) to rats on days 6 through 17 of gestation caused an increase in post-implantation mortality. This dose also caused an increase in total fetal malformations. The most frequent malformations were of the eye (microphthalmia, anophthalmia, rosette formation of the retina, coloboma of the retina, ectopic orbit), brain (dilated lateral and third ventricles), skull, and vertebrae.

8.2 Lactation

Risk Summary

There are no data on the presence of topotecan or its metabolites in human milk, or their effects on the breastfed infant or milk production. Lactating rats excrete high concentrations of topotecan into milk (see Data). Because of the potential for serious adverse reactions in breastfed infants, advise women not to breastfeed during treatment with HYCAMTIN and for 1 week after the last dose.

Data

Following intravenous administration of topotecan to lactating rats at a dose of 4.72 mg/m^2 (about twice the 1.5 mg/m^2 clinical intravenous dose based on BSA), topotecan was excreted into milk at concentrations up to 48-fold higher than those in plasma.

8.3 Females and Males of Reproductive Potential

Pregnancy Testing

Verify pregnancy status of females of reproductive potential prior to initiating HYCAMTIN capsules [see Use in Specific Populations (8.1)].

Contraception

HYCAMTIN can cause fetal harm when administered to a pregnant woman [see Use in Specific Populations (8.1)].

Females

Advise female patients of reproductive potential to use effective contraception during treatment with HYCAMTIN capsules and for 6 months after the last dose.

Males

HYCAMTIN capsules may damage spermatozoa, resulting in possible genetic and fetal abnormalities. Advise males with a female partner of reproductive potential to use effective contraception during treatment with HYCAMTIN capsules and for 3 months after the last dose [see Nonclinical Toxicology (13.1)].

Infertility

Females

HYCAMTIN can have both acute and long-term effects on fertility [see Nonclinical Toxicology (13.1)].

Males

Effects on spermatogenesis have occurred in animals administered topotecan [see Nonclinical Toxicology (13.1)].

8.4 Pediatric Use

Safety and effectiveness in pediatric patients have not been established.

8.5 Geriatric Use

Of the 682 patients with lung cancer who received HYCAMTIN capsules in the four clinical trials, 33% were aged 65 years and older, while 4.8% were aged 75 years and older. Treatment-related diarrhea was more frequent in patients aged greater than or equal to 65 years (28%) compared with those younger than 65 years (19%) [see Warnings and Precautions (5.2), Adverse Reactions (6.1)]. No overall differences in effectiveness were observed between patients 65 years and older and younger patients.

8.6 Renal Impairment

No dosage adjustment is recommended for patients with creatinine clearance (CLcr) greater than or equal to 50 mL/min. Reduce the dose of HYCAMTIN capsules in patients with CLcr less than 49 mL/min [see Dosage and Administration (2.3), Clinical Pharmacology (12.3)].

10 OVERDOSAGE

Overdoses (up to 5-fold of the prescribed dose) have occurred in patients receiving HYCAMTIN capsules. The primary complication of overdosage is myelosuppression. Mucositis have occurred with overdosages. If an overdose is suspected, monitor the patient closely for myelosuppression and institute supportive-care measures as appropriate.

11 DESCRIPTION

Topotecan is a topoisomerase inhibitor. The chemical name for topotecan hydrochloride is (S)-10-[(dimethylamino)methyl]-4-ethyl-4,9-dihydroxy-1H-pyrano[3',4':6,7] indolizino [1,2-b]quinoline-3,14-(4H,12H)-dione monohydrochloride. The molecular formula is C23H23N3O5•HCl and the molecular weight is 457.9 g/mol. It is soluble in water and melts with decomposition at 213°C to 218°C.

Topotecan hydrochloride has the following structural formula:

HYCAMTIN capsules, contain topotecan hydrochloride, the content of which is expressed as topotecan free base. Each 0.25 mg and 1 mg capsule contain topotecan hydrochloride equivalent to 0.25 mg and 1 mg topotecan free-base, respectively. The excipients are gelatin, glyceryl monostearate, hydrogenated vegetable oil, and titanium dioxide. The capsules are imprinted with edible black ink. The 1 mg capsules also contain red iron oxide.

12 CLINICAL PHARMACOLOGY

12.1 Mechanism of Action

Topoisomerase I relieves torsional strain in DNA by inducing reversible single-strand breaks. Topotecan binds to the topoisomerase I-DNA complex and prevents re-ligation of these single-strand breaks. The cytotoxicity of topotecan is thought to be due to double-strand DNA damage produced during DNA synthesis, when replication enzymes interact with the ternary complex formed by topotecan, topoisomerase I, and DNA. Mammalian cells cannot efficiently repair these double-strand breaks.

12.3 Pharmacokinetics

Following administration of HYCAMTIN capsules at doses of 1.2 to 3.1 mg/m^2 (0.52 to 1.35 times the recommended dose) administered daily for 5 days, the area under the curve (AUC) increased proportionally with dose.

Absorption

The time to the peak plasma concentrations is between 1 to 2 hours following oral administration. The oral bioavailability of topotecan is approximately 40%.

Food Effect

Following a high-fat meal, the AUC was similar in the fed and fasted states, while Tmax was delayed from 1.5 to 3 hours for topotecan lactone and from 3 to 4 hours for total topotecan.

Distribution

Protein binding of topotecan is approximately 35%.

Elimination

The mean terminal half-life (t½) of topotecan is 3 to 6 hours following oral administration.

Metabolism

Topotecan undergoes a reversible pH-dependent hydrolysis of a pharmacologically active lactone moiety. At pH less than or equal to 4, the lactone is exclusively present, whereas the ring-opened hydroxy-acid form predominates at physiologic pH. The mean metabolite: parent AUC ratio was less than 10% for total topotecan and topotecan lactone.

Excretion

The overall recovery of drug-related material following 5 daily doses of topotecan was 57% of the administered oral dose. In the urine, 20% of the orally administered dose was excreted as total topotecan and 2% was excreted as N-desmethyl topotecan. Fecal elimination of total topotecan accounted for 33%, while fecal elimination of the active metabolite N-desmethyl topotecan accounted for 1.5%. Overall, the N-desmethyl metabolite contributed a mean of less than 6% (range: 4% to 8%) of the total drug-related material accounted for in the urine and feces.

Specific Populations

No clinically significant differences in the pharmacokinetics of topotecan were observed based on age, sex, or hepatic impairment following oral administration.

Racial and Ethnic Groups

In patients with creatinine clearance (CLcr) greater than 80 mL/min, the dose-normalized AUCinf to topotecan lactone and total topotecan each were approximately 30% higher in Asians compared to Whites

Patients with Renal Impairment

The mean dose-normalized for total topotecan and topotecan lactone AUCinf increased in advanced cancer patients with renal impairment compared to patients with CLcr greater than 80 mL/min as presented in Table 2 [see Dosage and Administration (2.3)]. Prior platinum-based chemotherapy had no effect on the systemic exposure to both total topotecan and topotecan lactone in patients with CLcr greater than 80 mL/min.

Table 2. AUCinf Increases Compared to Normal Renal Function
Renal Impairment | Geometric Mean Dose-Normalized AUCinf
 | Total Topotecan | Topotecan Lactone
Whites
CLcr 50-79 mL/min CLcr 30-49 mL/min < 30 mL/min | 70% 108% 227% | 34% 80% 114%
Asians
CLcr 50-79 mL/min CLcr 30-49 mL/min < 30 mL/min | 26% 153% 331% | 34% 121% 247%

Drug Interaction Studies

Clinical Studies

Effect of P-glycoprotein (P-gp) and Breast Cancer Resistance Protein (BCRP) Inhibitors

Following coadministration of escalating doses of a dual inhibitor of BCRP and P-gp, the AUCinf of topotecan lactone and total topotecan increased approximately 2.5-fold compared to topotecan alone [see Drug Interactions (7.1)].

Coadministration of single oral dose of cyclosporine A (15 mg/kg), an inhibitor of P-gp, multidrug-resistance-associated protein (MRP-1) and CYP3A4, within 4 hours of oral topotecan increased the dose-normalized AUC0-24h of topotecan lactone and total topotecan 2- to 3-fold compared to topotecan alone [see Drug Interactions (7.1)].

Effect of Gastric Acid Reducing Agents

No clinically significant changes in the pharmacokinetics of oral topotecan were observed when coadministered with ranitidine, a histamine-2 receptor antagonist.

In Vitro Studies

Topotecan does not inhibit CYP1A2, CYP2A6, CYP2C8/9, CYP2C19, CYP2D6, CYP2E, CYP3A, CYP4A, or dihydropyrimidine dehydrogenase.

13 NONCLINICAL TOXICOLOGY

13.1 Carcinogenesis, Mutagenesis, Impairment of Fertility

Carcinogenicity testing of topotecan has not been done. Nevertheless, topotecan is known to be genotoxic to mammalian cells and is a probable carcinogen. Topotecan was mutagenic to L5178Y mouse lymphoma cells and clastogenic to cultured human lymphocytes with and without metabolic activation. It was also clastogenic to mouse bone marrow. Topotecan did not cause mutations in bacterial cells.

Topotecan given to female rats prior to mating at an intravenous dose of 1.4 mg/m^2 [(about 0.6 times the 2.3 mg/m^2 oral clinical dose based on body surface area (BSA)] caused superovulation possibly related to inhibition of follicular atresia. This dose given to pregnant female rats also caused increased pre-implantation loss. Studies in dogs given an intravenous dose of 0.4 mg/m^2 (about 0.2 times the 2.3 mg/m^2 oral clinical dose based on BSA) of topotecan daily for a month suggest that treatment may cause an increase in the incidence of multinucleated spermatogonial giant cells in the testes.

14 CLINICAL STUDIES

14.1 Small Cell Lung Cancer (SCLC)

The efficacy of HYCAMTIN capsules was studied in 141 patients with relapsed SCLC in a randomized, controlled, open-label trial (Study 478). The patients were prior responders (complete or partial) to first-line chemotherapy, were not considered candidates for standard intravenous chemotherapy and had relapsed at least 45 days from the end of first-line chemotherapy. Patients were randomized 1:1 to HYCAMTIN capsules (2.3 mg/m^2 orally once daily for 5 consecutive days, starting on Day 1 of a 21-day cycle) with best supportive care (BSC) or BSC alone. The major efficacy outcome measure was overall survival (OS).

Patients randomized to HYCAMTIN capsules with BSC received a median of 4 courses (range: 1 to 10) and maintained a median dose intensity of 3.77 mg/m^2/week. The median patient age in patients receiving HYCAMTIN capsules with BSC and BSC alone was 60 years and 58 years, while the percentage of patients aged greater than or equal to 65 years was 34% and 29%, respectively. The majority of patients were White (99%) and male (73%). In the HYCAMTIN capsules with BSC arm, 68% of patients had extensive disease and 28% had liver metastasis. In the BSC alone arm, 61% had extensive disease and 20% had liver metastases. Eighty percent of patients receiving HYCAMTIN capsules with BSC previously received carboplatin or cisplatin and 77% of patients in the BSC alone arm received prior carboplatin or cisplatin. In the arm receiving HYCAMTIN capsules with BSC, 18% of patients had prior carboplatin and 62% had prior cisplatin. In the BSC-alone arm, 26% of patients had prior carboplatin and 51% had prior cisplatin.

The arm receiving HYCAMTIN capsules with BSC showed a statistically significant improvement in OS compared with the BSC-alone arm (Log-rank P = 0.0104). Efficacy results are shown in Table 3 and Figure 1.

Table 3. Efficacy Results in Small Cell Lung Cancer in Study 478
Parameters | Treatment Group
Parameters | HYCAMTIN Capsules with BSC | BSC
Parameters | (N = 71) | (N = 70)
Median Overall Survival (months) (95% CI) | 6.0 (4.2, 7.3) | 3.2 (2.6, 4.3)
Hazard ratio (95% CI) | 0.64 (0.45, 0.90)
Log-rank P-value | 0.0104

Abbreviations: BSC, Best Supportive Care; N, Total number of patients randomized; CI, Confidence Interval.

Figure 1. Kaplan-Meier Curves for Overall Survival in Small Cell Lung Cancer in Study 478

15 REFERENCES

1. “OSHA Hazardous Drugs.” OSHA. http://www.osha.gov/SLTC/hazardousdrugs/index.html.

16 HOW SUPPLIED/STORAGE AND HANDLING

The 0.25 mg HYCAMTIN capsules are opaque white to yellowish-white imprinted with HYCAMTIN and 0.25 mg and are available in bottles of 10: NDC 66758-101-11.

The 1 mg HYCAMTIN capsules are opaque pink imprinted with HYCAMTIN and 1 mg and are available in bottles of 10: NDC 66758-102-11.

Store refrigerated 2ºC to 8ºC (36ºF to 46ºF) protected from light in the original carton.

HYCAMTIN is a cytotoxic drug. Follow applicable special handling and disposable procedures.^1

17 PATIENT COUNSELING INFORMATION

Advise the patient to read the FDA-approved patient labeling (Patient Information).

Myelosuppression

Inform patients that HYCAMTIN decreases blood cell counts, such as white blood cells, platelets, and red blood cells. Instruct patients to notify their healthcare provider promptly for fever or other signs of infection [see Warnings and Precautions (5.1)].

Diarrhea

Inform patients that HYCAMTIN capsules can cause diarrhea which may be severe and life-threatening. Instruct patients how to manage and/or prevent diarrhea and to inform their physician if severe diarrhea occurs during treatment with HYCAMTIN capsules [see Warnings and Precautions (5.2)].

Interstitial Lung Disease (ILD)

Inform patients of the risks of severe ILD. Advise patients to contact their healthcare provider immediately to report new or worsening respiratory symptoms [see Warnings and Precautions (5.3)].

Embryo-Fetal Toxicity

Advise females of reproductive potential and males with female partners of reproductive potential of the potential risk to a fetus. Advise women to contact their healthcare provider if they become pregnant, or if pregnancy is suspected during treatment with HYCAMTIN capsules [see Warnings and Precautions (5.4), Use in Specific Populations (8.1, 8.3)].

Advise females of reproductive potential to use effective contraception during treatment and for 6 months after the last dose of HYCAMTIN capsules [see Use in Specific Populations (8.1, 8.3)].

Advise males with a female partner of reproductive potential to use effective contraception during treatment and for 3 months after the last dose of HYCAMTIN capsules [see Use in Specific Populations (8.1, 8.3), Nonclinical Toxicology (13.1)].

Lactation

Advise women to discontinue breastfeeding during treatment and for 1 week after the last dose of HYCAMTIN capsules [see Use in Specific Populations (8.2)].

Infertility

Advise male and female patients of the potential risk for impaired fertility [see Use in Specific Populations (8.3), Nonclinical Toxicology (13.1)].

Manufactured by:

GlaxoSmithKline Manufacturing S.p.A.

San Polo di Torrile, Parma, Italy for

Sandoz Inc., Princeton, NJ 08540

PATIENT INFORMATION
HYCAMTIN® (hi-CAM-tin)
(topotecan) capsules

What is the most important information I should know about HYCAMTIN?
HYCAMTIN may cause serious side effects, including:

- Bone marrow problems. HYCAMTIN can affect your bone marrow and can cause a severe decrease in your white blood cell, red blood cell, and platelet counts. Decreased blood cell counts can make you more likely to develop bleeding, bruising, anemia, or infections which may be life-threatening. Your healthcare provider will do blood tests regularly to check your blood cell counts during treatment with HYCAMTIN. Tell your healthcare provider right away if you have any signs of infection, including:
  - fever (temperature of 100.5°F or greater)
  - chills
  - cough
  - burning or pain on urination
- Diarrhea. HYCAMTIN can cause severe and life-threatening diarrhea that may need to be treated in a hospital. Tell your healthcare provider right away if you develop:
  - diarrhea with fever
  - diarrhea 3 or more times a day
  - diarrhea with stomach-area pain or cramps

See “What are the possible side effects of HYCAMTIN?” for more information about side effects.

What is HYCAMTIN?
  HYCAMTIN is a prescription medicine used to treat small cell lung cancer (SCLC) that has come back (relapsed) and:
2. the cancer responded to your first chemotherapy, and
3. it has been at least 45 days from the last dose of chemotherapy

It is not known if HYCAMTIN is safe and effective in children.

Do not take HYCAMTIN if you are allergic to topotecan or any of the ingreidents in HYCAMTIN. See the end of this leaflet for a complete list of ingredients in HYCAMTIN.

Before taking HYCAMTIN, tell your healthcare provider about all of your medical conditions, including if you:

- have diarrhea or watery stools
- have or have had lung problems
- have kidney problems
- are pregnant or plan to become pregnant. HYCAMTIN can harm your unborn baby.
  - Females who are able to become pregnant should use effective birth control (contraception) during treatment with HYCAMTIN and for 6 months after the last dose of HYCAMTIN.
  - Males who have female partners who are able to become pregnant, should use effective birth control during treatment with HYCAMTIN and for 3 months after the last dose of HYCAMTIN.
  - Talk to your healthcare provider about birth control methods that may be right for you during treatment with HYCAMTIN.
  - Your healthcare provider will do a pregnancy test before you start taking HYCAMTIN. Tell your healthcare provider right away if you become pregnant, think you might be pregnant, or your female partner becomes pregnant during treatment with HYCAMTIN.
- are breastfeeding or plan to breastfeed. It is not known if HYCAMTIN passes into your breast milk. Do not breastfeed during treatment with HYCAMTIN and for 1 week after the last dose. Talk to your healthcare provider about the best way to feed your baby during this time.

Tell your healthcare provider about all the medicines you take, including prescription and over-the-counter medicines, vitamins, and herbal supplements.

Taking HYCAMTIN with certain other medicines can affect how HYCAMTIN works causing side effects.

Know the medicines you take. Keep a list of them to show your healthcare provider and pharmacist when you get a new medicine.

How should I take HYCAMTIN?

- Take HYCAMTIN exactly as your healthcare provider tells you to take it.
- Your healthcare provider will tell you how many HYCAMTIN capsules to take and when to take them. Your healthcare provider may change your dose if needed.
- Your healthcare provider may want you to take both 1 mg and 0.25 mg HYCAMTIN capsules for your prescribed dose. It is important for you to be able to tell the difference between the capsules. The 1-mg capsule is a pink color and the 0.25 mg capsule is a white to yellowish-white color.
- Take HYCAMTIN one time a day for 5 days in a row. This treatment will normally be repeated every 3 weeks (a treatment cycle). Your healthcare provider will decide how long you will take HYCAMTIN.
- Take HYCAMTIN with or without food.
- Swallow HYCAMTIN whole. Do not open, chew, crush, or divide HYCAMTIN.
- If any of the HYCAMTIN capsules are broken or leaking, do not touch them with your bare hands. Carefully throw away (dispose of) the capsules, and then wash your hands well with soap and water.
- If you get any of the contents of HYCAMTIN capsules on your skin or in your eyes, do the following:
  ° Wash the area of skin well with soap and water right away.
  ° Wash your eyes right away with gently flowing water for at least 15 minutes.
  ° Call your healthcare provider if you get a skin reaction or get HYCAMTIN in your eyes.
- If you take too much HYCAMTIN, call your healthcare provider right away.
- If you miss a dose of HYCAMTIN, or if you vomit after taking your HYCAMTIN, take your next dose at the next scheduled time. Do not take another dose on the same day.

What are the possible side effects of HYCAMTIN?
HYCAMTIN may cause serious side effects, including:

- See “What is the most important information I should know about HYCAMTIN?”
- Lung problems that can cause death. Tell your healthcare provider right away if you have new or worse symptoms of coughing, fever, shortness of breath, or problems breathing. Your healthcare provider may tell you to stop taking HYCAMTIN capsules.

The most common side effects of HYCAMTIN include:

• decreased blood cell counts
  • diarrhea
  • hair loss

• nausea
  • vomiting
  • fatigue

Your healthcare provider may tell you to decrease your dose, temporarily stop, or completely stop taking HYCAMTIN if you develop certain serious side effects during treatment with HYCAMTIN.

HYCAMTIN may cause short-term and long-term fertility problems in females. This could affect your ability to become pregnant.

HYCAMTIN may cause lower sperm count problems in men. This could affect your ability to father a child and cause birth defects. Talk to your healthcare provider about family planning options that might be right for you.

These are not all the possible side effects of HYCAMTIN.

Call your doctor for medical advice about side effects. You may report side effects to FDA at 1-800-FDA-1088.

How should I store HYCAMTIN?

- Store HYCAMTIN in a refrigerator between 36°F to 46°F (2°C to 8°C).
- Keep the bottle of HYCAMTIN in the carton that it comes in to protect it from light.
- Ask your healthcare provider or pharmacist how to safely throw away any unused or expired HYCAMTIN.

Keep HYCAMTIN and all medicines out of the reach of children.

General information about the safe and effective use of HYCAMTIN
Medicines are sometimes prescribed for purposes other than those listed in a Patient Information leaflet. Do not use HYCAMTIN for a condition for which it was not prescribed. Do not give HYCAMTIN to other people, even if they have the same symptoms that you have. It may harm them. You can ask your pharmacist or healthcare provider for information about HYCAMTIN that is written for health professionals.

What are the ingredients in HYCAMTIN?
  Active ingredient: topotecan hydrochloride
  Inactive ingredients: gelatin, glyceryl monostearate, hydrogenated vegetable oil, and titanium dioxide. The 1-mg capsules also contain red iron oxide. The capsules are imprinted with edible black ink.
  Manufactured by:

GlaxoSmithKline Manufacturing S.p.A.

San Polo di Torrile, Parma, Italy for

Sandoz Inc., Princeton, NJ 08540

731516
  For more information go to www.sandoz.com or call 1-800-525-8747.

This Patient Information has been approved by the U.S. Food and Drug Administration.

Revised: 9/2023

PACKAGE LABEL

Principal Display Panel

NDC 66758-101-11

HYCAMTIN®

(topotecan) Capsules

0.25 mg

Rx only

10 Capsules

Sandoz

PACKAGE LABEL

Principal Display Panel

NDC 66758-102-11

HYCAMTIN®

(topotecan) Capsules

1 mg

Rx only

10 Capsules

Sandoz